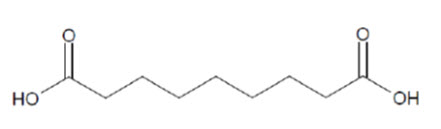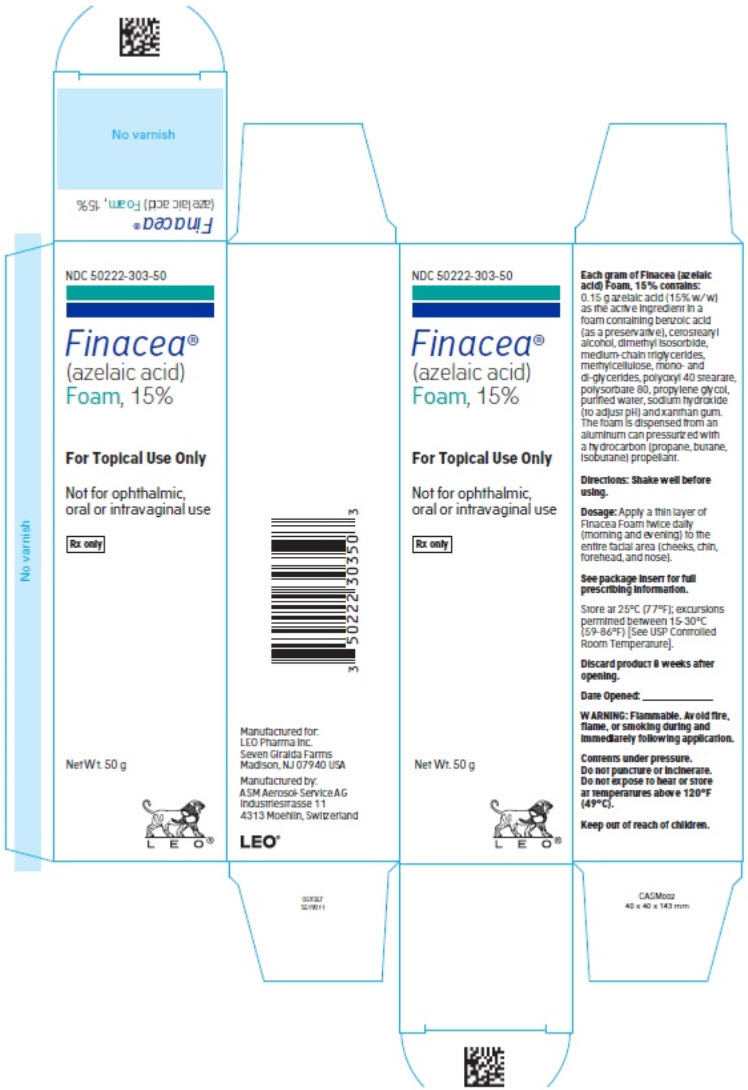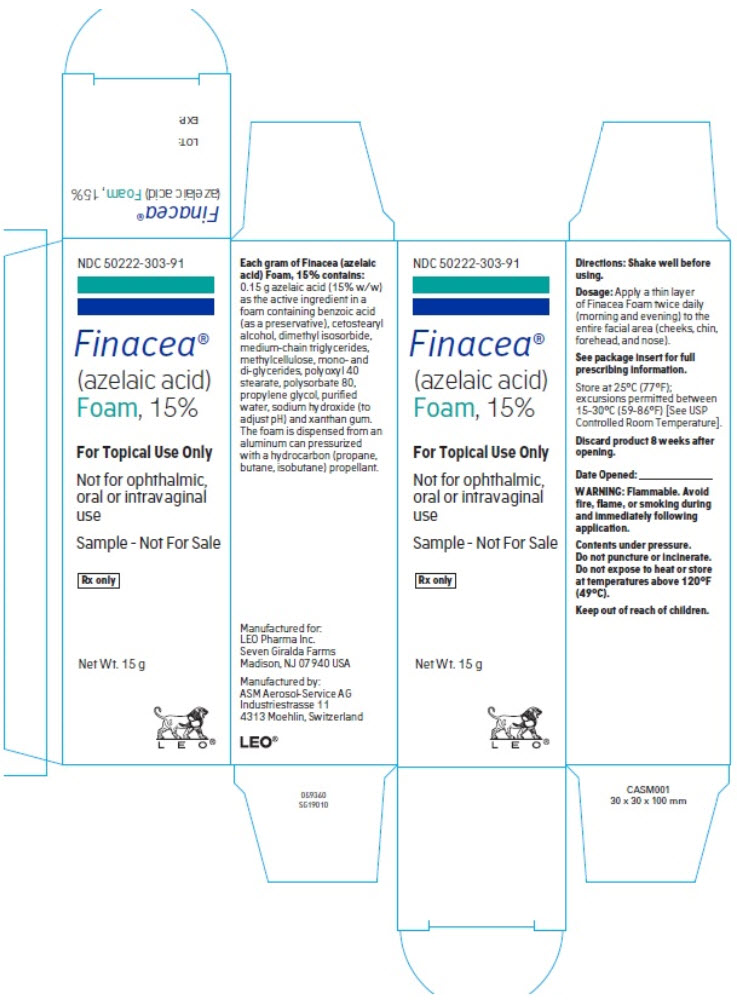 DRUG LABEL: FINACEA FOAM
NDC: 50222-303 | Form: AEROSOL, FOAM
Manufacturer: LEO Pharma Inc.
Category: prescription | Type: HUMAN PRESCRIPTION DRUG LABEL
Date: 20201208

ACTIVE INGREDIENTS: AZELAIC ACID .15 g/1 g
INACTIVE INGREDIENTS: BENZOIC ACID; CETOSTEARYL ALCOHOL; DIMETHYL ISOSORBIDE; GLYCERYL MONO AND DIPALMITOSTEARATE; MEDIUM-CHAIN TRIGLYCERIDES; METHYLCELLULOSE (4000 MPA.S); POLYOXYL 40 STEARATE; POLYSORBATE 80; PROPYLENE GLYCOL; SODIUM HYDROXIDE; WATER; XANTHAN GUM

HIGHLIGHTS OF PRESCRIBING INFORMATION

These highlights do not include all the information needed to use FINACEA Foam safely and effectively. See full prescribing information for FINACEA Foam.
FINACEA® (azelaic acid) foam, for topical use
Initial U.S. Approval: 1995

1 INDICATIONS AND USAGE

FINACEA Foam is indicated for the topical treatment of inflammatory papules and pustules of mild to moderate rosacea. (1)

2 DOSAGE AND ADMINISTRATION

- Apply a thin layer twice daily (morning and evening) to the entire facial area (cheeks, chin, forehead, and nose). (2)
- Use only very mild soaps or soapless cleansing lotion and pat dry with a soft towel before applying FINACEA Foam. (2)
- Wash hands immediately following application. (2)
- Cosmetics may be applied after the application of FINACEA Foam has dried. (2)
- Avoid use of alcoholic cleansers, tinctures and astringents, abrasives and peeling agents. (2)
- For topical use. (2)
- Not for oral, ophthalmic or intravaginal use. (2)

3 DOSAGE FORMS AND STRENGTHS

Foam, 15% (3)

4 CONTRAINDICATIONS

None. (4)

5 WARNINGS AND PRECAUTIONS

- Hypopigmentation: Isolated cases of hypopigmentation occurred after azelaic acid use. Monitor patients with dark complexion for early signs of hypopigmentation (5.1)
- Eye and Mucous Membrane Irritation: Azelaic acid has been reported to cause irritation of the eyes. Avoid contact with the eyes and mucous membranes. (5.2)
- Flammability: Contents are flammable. Instruct the patient to avoid fire, flame, and smoking during and immediately following application. (5.3)

6 ADVERSE REACTIONS

The most common adverse reactions (incidence ≥ 0.5% of subjects treated with FINACEA Foam) are local site pain (6.2%), pruritus (2.5%), dryness (0.7%), and erythema (0.7%). (6.1)

To report SUSPECTED ADVERSE REACTIONS, contact LEO Pharma Inc. at 1-877-494-4536 or FDA at 1-800-FDA-1088 or www.fda.gov/medwatch.

FULL PRESCRIBING INFORMATION

1 INDICATIONS AND USAGE

FINACEA Foam, 15% is indicated for topical treatment of the inflammatory papules and pustules of mild to moderate rosacea.

2 DOSAGE AND ADMINISTRATION

- Shake well before use.
- Cleanse affected area(s) using only very mild soaps or soapless cleansing lotion and pat dry with a soft towel before application of FINACEA Foam.
- Apply FINACEA Foam twice daily (morning and evening) to the entire facial area (cheeks, chin, forehead, and nose). For a single application, dispense the smallest amount of foam necessary to adequately cover the affected area(s) with a thin layer.
- Use FINACEA Foam continuously over 12 weeks.
- Wash hands immediately following application of FINACEA Foam.
- Cosmetics may be applied after the application of FINACEA Foam has dried.
- Reassess the diagnosis if no improvement is observed upon completing 12 weeks of therapy.
- Avoid the use of occlusive dressings or wrappings.
- Instruct patients to avoid use of alcoholic cleansers, tinctures and astringents, abrasives and peeling agents.
- For topical use.
- Not for oral, ophthalmic or intravaginal use.

3 DOSAGE FORMS AND STRENGTHS

Each gram of FINACEA (azelaic acid) Foam contains 0.15 g of azelaic acid (15% w/w) in a white to off-white foam.

4 CONTRAINDICATIONS

None.

5 WARNINGS AND PRECAUTIONS

5.1 Hypopigmentation

There have been reports of hypopigmentation after use of azelaic acid. Because azelaic acid has not been well studied in patients with dark complexion, monitor these patients for early signs of hypopigmentation.

5.2 Eye and Mucous Membranes Irritation

Azelaic acid has been reported to cause irritation of the eyes. Avoid contact with the eyes, mouth and other mucous membranes. If FINACEA Foam does come in contact with the eyes, wash the eyes with large amounts of water and consult a physician if eye irritation persists.

5.3 Flammability

The propellant in FINACEA Foam is flammable. Instruct the patient to avoid fire, flame, and smoking during and immediately following application. Do not puncture and/or incinerate the containers. Do not expose containers to heat and/or store at temperatures above 120°F (49°C).

6 ADVERSE REACTIONS

The following adverse reactions are described elsewhere in the prescribing information:

- Hypopigmentation [see Warnings and Precautions (5.1)].
- Eye and Mucous Membranes Irritation [see Warnings and Precautions (5.2)].

6.1 Clinical Trials Experience

Because clinical trials are conducted under widely varying conditions, adverse reaction rates observed in the clinical trials of a drug cannot be directly compared to rates in the clinical trials of another drug and may not reflect the rates observed in practice.

FINACEA Foam was evaluated for the treatment of papulopustular rosacea in two multicenter, randomized, double-blind, vehicle-controlled, 12-week clinical trials involving a total of 1362 (FINACEA Foam, 15%: 681; vehicle: 681) subjects. Overall, 95.7% of subjects were White, 73.4% were female, and the mean age was 50.6 years.

Table 1: Adverse Reactions Occurring in ≥ 0.5% of Subjects Treated with FINACEA Foam Compared with Subjects Treated with Vehicle
System/Organ Class Preferred | FINACEA Foam, 15% (N=681) n (%) | Vehicle (N=681) n (%)
General disorders and application site conditions
Application site pain ["Application site pain" is a term used to describe disagreeable skin sensations, including burning, stinging, paraesthesia and tenderness.] | 42 (6.2%) | 10 (1.5%)
Application site pruritus | 17 (2.5%) | 2 (0.3%)
Application site dryness | 5 (0.7%) | 5 (0.7%)
Application site erythema | 5 (0.7%) | 6 (0.9%)

Local Tolerability Studies

In a 21-day cumulative irritation study under occlusive conditions, mild-to-moderate irritation was observed for azelaic acid pre-foam emulsion. In a human repeat insult patch test (HRIPT) study, no sensitization potential was observed for azelaic acid pre-foam emulsion.

6.2 Postmarketing Experience

Hypersensitivity, rash and worsening of asthma have been reported from the postmarketing experience of azelaic acid-containing formulations. Because these reactions are reported voluntarily from a population of uncertain size, it is not always possible to reliably estimate their frequency or establish a causal relationship to drug exposure.

8 USE IN SPECIFIC POPULATIONS

8.1 Pregnancy

Risk Summary

Azelaic acid is minimally absorbed systemically following topical route of administration, and maternal use is not expected to result in fetal exposure to the drug [see Clinical Pharmacology (12.3)].

In animal reproduction studies, embryofetal toxicity was noted when azelaic acid was administered orally during the period of organogenesis at doses 162, 19, and 65 times the maximum recommended human dose (MRHD) in rats, rabbits, and monkeys, respectively. Maternal toxicity was noted at these doses but no malformations were observed in these embryofetal developmental studies (see Data).

The background risk of major birth defects and miscarriage for the indicated population is unknown. All pregnancies have a background risk of birth defect, loss, or other adverse outcomes. In the U.S. general population, the estimated background risk of major birth defects and miscarriage in clinically recognized pregnancies is 2 to 4% and 15 to 20%, respectively.

Data

Animal Data

Dermal embryofetal developmental toxicology studies have not been performed with azelaic acid, 15% foam. Oral embryofetal developmental studies were conducted with azelaic acid in rats, rabbits, and cynomolgus monkeys. Azelaic acid was administered during the period of organogenesis in all three animal species. Embryotoxicity was observed in rats, rabbits, and monkeys at oral doses of azelaic acid that generated some maternal toxicity. Embryotoxicity was observed in rats given 2500 mg/kg/day [162 times the MRHD based on body surface area (BSA) comparison], rabbits given 150 or 500 mg/kg/day (19 or 65 times the MRHD based on BSA comparison) and cynomolgus monkeys given 500 mg/kg/day (65 times the MRHD based on BSA comparison) azelaic acid. No malformations were observed in the oral embryofetal developmental studies conducted in rats, rabbits and cynomolgus monkeys.

An oral peri- and post-natal developmental study was conducted in rats. Azelaic acid was administered from gestational day 15 through day 21 postpartum up to a dose level of 2500 mg/kg/day. Embryotoxicity was observed in rats at an oral dose of 2500 mg/kg/day (162 times the MRHD based on BSA comparison) that generated some maternal toxicity. In addition, slight disturbances in the post-natal development of fetuses was noted in rats at oral doses that generated some maternal toxicity (500 and 2500 mg/kg/day; 32 and 162 times the MRHD based on BSA comparison). No effects on sexual maturation of the fetuses were noted in this study.

8.2 Lactation

Risk Summary

Azelaic acid is naturally present in human milk. When used as prescribed, azelaic acid is unlikely to be absorbed through the skin in clinically relevant amounts to cause a change in azelaic acid concentration in milk or milk production; therefore, breastfeeding is not expected to result in exposure of the infant to FINACEA Foam. The developmental and health benefits of breastfeeding should be considered along with the mother's clinical need for FINACEA Foam and any potential adverse effects on the breastfed child from FINACEA Foam or from the underlying maternal condition.

8.4 Pediatric Use

The safety and efficacy of FINACEA Foam have not been established in pediatric patients.

8.5 Geriatric Use

Of the total number of subjects in clinical studies of FINACEA Foam, 18.8 percent were 65 and over, while 7.2 percent were 75 and over. No overall differences in safety or effectiveness were observed between these subjects and younger subjects, and other reported clinical experience has not identified differences in responses between the elderly and younger patients, but greater sensitivity of some older individuals cannot be ruled out.

11 DESCRIPTION

FINACEA (azelaic acid) Foam contains 15% (w/w) azelaic acid, a naturally-occurring saturated dicarboxylic acid and is suspended in an oil-in-water emulsion vehicle. It is for topical use. Chemically, azelaic acid is 1,7-heptanedicarboxylic acid. The structural formula of azelaic acid is:

Azelaic acid has a molecular formula of C9 H16 O4 and a molecular weight of 188.22.

The aluminum containers are filled with hydrophilic emulsion, crimped with a continuous spray valve, and pressurized with propellants consisting of propane, butane, and isobutane. Each gram of FINACEA Foam, 15% contains 0.15 g of azelaic acid. FINACEA Foam also contains benzoic acid (as a preservative), cetostearyl alcohol, dimethyl isosorbide, medium-chain triglycerides, methylcellulose, mono- and di-glycerides, polyoxyl 40 stearate, polysorbate 80, propylene glycol, purified water, sodium hydroxide (to adjust pH), and xanthan gum as inactive ingredients.

12 CLINICAL PHARMACOLOGY

12.1 Mechanism of Action

The mechanism(s) by which azelaic acid interferes with the pathogenic events in rosacea are unknown.

12.2 Pharmacodynamics

The efficacy of FINACEA Foam is being driven by local mechanisms of azelaic acid within the skin.

12.3 Pharmacokinetics

Pharmacokinetics of azelaic acid and its metabolite pimelic acid was assessed in 21 adult subjects with moderate papulopustular rosacea with a minimum of 15 and no more than 50 inflammatory lesions (papules and/or pustules). Endogenous plasma concentrations of azelaic acid (range <1-105 ng/mL) and pimelic acid (range 0.69-27 ng/mL) were measured over various time points over 2 days prior to treatment initiation. The endogenous plasma concentrations varied widely across subjects and the mean ± SD values of endogenous azelaic acid plasma concentrations ranged between 4.5 ± 2.4 ng/mL and 14.6 ± 5.6 ng/mL and pimelic acid plasma concentrations ranged between 2.2 ± 1.1 ng/mL and 3.7 ± 3.1 ng/mL.

Following topical dermal applications of a mean dose of 0.94 g of FINACEA Foam (141 mg azelaic acid) twice daily for 7 consecutive days, systemic concentrations of azelaic acid were at steady state by Day 5. On Day 7, a wide range of maximum azelaic acid (22.2 to 90.1 ng/mL) and pimelic acid (2.3-16.9 ng/mL) plasma concentrations (Cmax) was also observed after treatment with FINACEA Foam. The mean ± SD Cmax for azelaic acid and pimelic acid were 51.8 ± 18.5 ng/mL and 5.0 ± 3.0 ng/mL, respectively. The mean ± SD systemic exposure of azelaic acid and pimelic acid within a dosing interval (AUC0-12h) were 442.0 ± 177.6 ng.h/mL and 43.4 ± 15.4 ng.h/mL, respectively.

Azelaic acid is mainly excreted unchanged in the urine, but undergoes some ß-oxidation to shorter chain dicarboxylic acids.

13 NONCLINICAL TOXICOLOGY

13.1 Carcinogenesis, Mutagenesis, Impairment of Fertility

In a 2-year dermal mouse carcinogenicity study, azelaic acid pre-foam emulsion was administered twice daily to CD-1 mice at topical doses of 5%, 15%, and 30% (500, 1500, and 3000 mg/kg/day azelaic acid). No drug-related tumors were noted at concentrations up to 30% azelaic acid (527 times the MRHD based on AUC comparison).

Azelaic acid was not mutagenic or clastogenic in a battery of in vitro [Ames assay, HGPRT assay in V79 cells (Chinese hamster lung cells), and chromosomal aberration assay in human lymphocytes] and in vivo (dominant lethal assay in mice and mouse micronucleus assay) genotoxicity tests.

Oral administration of azelaic acid at dose levels up to 2500 mg/kg/day (162 times the MRHD based on BSA comparison) did not affect fertility or reproductive performance in male or female rats.

14 CLINICAL STUDIES

The efficacy and safety of FINACEA Foam was evaluated in two multicenter, randomized, double-blind, vehicle-controlled, 12-week clinical trials (Trials 1 and 2) in subjects with papulopustular rosacea, with a mean lesion count of 21.3 (range 12 to 50) inflammatory papules and pustules. A total of 1362 (active: 681; vehicle: 681) subjects aged 19 to 92 years (mean age = 50.6 years), 95.7% Caucasian, and 73.4% female participated in the trials. The following subjects were excluded: a) those with ocular rosacea, phymatous rosacea or plaque-type rosacea lesions; b) those with rosacea that requires systemic treatment; c) those who are known non-responders to azelaic acid, and d) those with a known hypersensitivity to any ingredients of the study drug. FINACEA Foam or its vehicle were to be applied twice daily for 12 weeks; no other topical or systemic medication affecting the course of rosacea and/or evaluability was to be used during the studies. Subjects were instructed to avoid any food and beverages that, by their own experience, may provoke erythema, flushing and blushing, including spicy food, hot drinks and alcoholic beverages during the study. Subjects were also instructed to avoid use of products which may cause local irritation such as soaps, alcohol-containing cleansers, tinctures and astringents, abrasives and peeling agents during the study.

The efficacy endpoints were 1) nominal change in inflammatory lesion count from baseline and 2) success defined as a score of "clear" or "minimal" with at least 2-step reduction from baseline on a 5-point Investigator's Global Assessment (IGA). Details on IGA are specified below:

Clear | no papules and/or pustules; no erythema
Minimal | rare papules and/or pustules; faint, up to but not including mild erythema
Mild | few papules and/or pustules; mild erythema
Moderate | pronounced number of papules and/or pustules, but less than numerous papules and/or pustules; moderate erythema
Severe | numerous papules and/or pustules, occasionally with confluent areas of inflamed lesions; moderate to severe erythema

FINACEA Foam was superior to its vehicle in the treatment of rosacea in reducing the number of inflammatory papules and pustules and demonstrating success according to IGA at the end of treatment (Table 2).

Table 2: IGA Success Rate and Nominal Change in Inflammatory Lesion Count from Baseline to End of the 12-Week Treatment Period
 | Trial 1 |  | Trial 2
 | FINACEA Foam, 15% | Vehicle | FINACEA Foam, 15% | Vehicle
 | N=483 | N=478 | N=198 | N=203
IGA success rate | 32.1% | 23.4% | 43.4% | 32.5%
Mean nominal change in inflammatory lesion count from baseline | -13.2 | -10.3 | -13.3 | -9.5

16 HOW SUPPLIED/STORAGE AND HANDLING

How Supplied

FINACEA (azelaic acid) Foam 15% is a white to off-white emulsion supplied in a pressurized 50 g (NDC 50222-303-50) aluminum can.

Storage and Handling

Store at 25◦C (77◦F); excursions permitted between 15–30◦C (59–86◦F) [See USP Controlled Room Temperature].

Flammable. Avoid fire, flame, or smoking during and immediately following application. Contents under pressure. Do not puncture or incinerate. Do not expose to heat or store at temperatures above 120°F (49°C).

17 PATIENT COUNSELING INFORMATION

Inform patients using FINACEA Foam of the following:

Administration Instructions

- For topical use only.
- Shake well before use.
- Before applying FINACEA Foam, cleanse affected area(s) with a very mild soap or a soapless cleansing lotion and pat dry with a soft towel.
- Wash hands immediately following application of FINACEA Foam.
- Cosmetics may be applied after the application of FINACEA Foam has dried.
- Avoid the use of occlusive dressings and wrappings.
- Avoid use of alcoholic cleansers, tinctures and astringents, abrasives and peeling agents.
- If allergic reactions occur, discontinue use and consult your physician.
- Discard product 8 weeks after opening [see Dosage and Administration (2)].

Hypopigmentation

- Advise patients to report abnormal changes in skin color to their healthcare provider [see Warnings and Precautions (5.1)].

Eye and Mucous Membranes Irritation

- Avoid contact with the eyes, mouth and other mucous membranes. If FINACEA Foam does come in contact with the eyes, wash the eyes with large amounts of water and consult your physician if eye irritation persists [see Warnings and Precautions (5.2)].

Flammability

- The propellant in FINACEA Foam is flammable. Avoid fire, flame, or smoking during and immediately following application [see Warnings and Precautions (5.3)].

FINACEA is a registered trademark of LEO Pharma A/S.
© 2020, LEO Pharma Inc. All rights reserved.

Manufactured for:

LEO Pharma Inc., Seven Giralda Farms, Madison, NJ 07940 USA

Manufactured by:

ASM Aerosol-Service AG, Industriestrasse 11, 4313 Moehlin, Switzerland

PRINCIPAL DISPLAY PANEL - 50 g Can Carton

NDC 50222-303-50

Finacea®
(azelaic acid)
Foam, 15%

For Topical Use Only

Not for ophthalmic,
oral or intravaginal use

Rx only

Net Wt. 50 g

LEO®

PRINCIPAL DISPLAY PANEL - 15 g Can Carton

NDC 50222-303-91

Finacea®
(azelaic acid)
Foam, 15%

For Topical Use Only

Not for ophthalmic,
oral or intravaginal
use

Sample - Not For Sale

Rx only

Net Wt. 15 g

LEO®